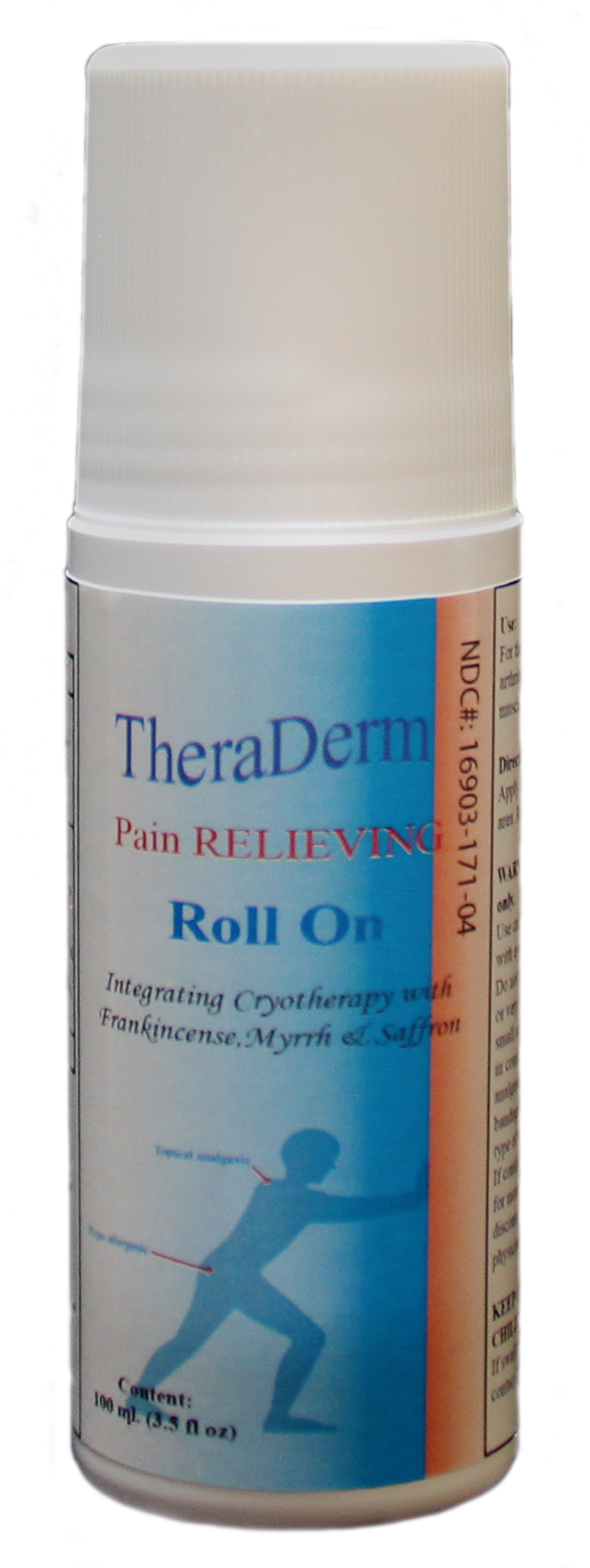 DRUG LABEL: Thera Derm Roll On
NDC: 16903-171 | Form: LIQUID
Manufacturer: Manna Omni International Incorporated
Category: otc | Type: HUMAN OTC DRUG LABEL
Date: 20180219

ACTIVE INGREDIENTS: METHYL SALICYLATE 2-ETHYLBUTYRATE 18 mg/90 mg; CAMPHOR (NATURAL) 4 mg/90 mg; PEPPERMINT OIL 9 mg/90 mg; MENTHOL 1-PROPYLENE GLYCOL CARBONATE, (-)- 9 mg/90 mg
INACTIVE INGREDIENTS: PRUNUS PERSICA FLOWER BUD 2 mg/90 mg; NOTOPTERYGIUM FRANCHETII ROOT 2 mg/90 mg; ANGELICA PUBESCENS ROOT 2 mg/90 mg; ZINGIBER CASSUMUNAR ROOT OIL 2 mg/90 mg; MYRRH 2 mg/90 mg; ALOE 2 mg/90 mg; SALVIA MILTIORRHIZA ROOT 2 mg/90 mg; CARTHAMUS TINCTORIUS FLOWER OIL 2 mg/90 mg; LAVENDER OIL 1 mg/90 mg; ANGELICA SINENSIS ROOT 2 mg/90 mg; LIGUSTICUM SINENSE SUBSP. CHUANXIONG ROOT 2 mg/90 mg; FRANKINCENSE OIL 2 mg/90 mg; STEARIC ACID 5 mg/90 mg; PHENOXYETHANOL 1 mg/90 mg; COCONUT OIL 2 mg/90 mg

Theraderm Pain Relieving Roll On

DOSAGE AND ADMINISTRATION

is to be used on sore muscles, for minor aches and pains. If pain persists for more than three days consult your doctor.Apply small amount onto affected area and repeat three (3) to four (4) times daily.

INDICATIONS AND USAGE

For the relief of minor aches and pains, muscles aches or sprains, and minor back or arthritis pain.

Warning: For External Use Only

Use only as directed. Avoid contact with the eyes and mucous membranes. Do not apply to wounds, damaged or very sensitive skin. Test on a small area before use. DO not use in combination with other analgesic products.DO not bandage tightly or cover with any type of wrap except clothing. If condition worsens, or persists for more than seven days, discontinue use and consult a physician.

Keep out of the Reach of Children

If swallowed,get medical help or contact Poision Control right away.

Active Ingredients:

Menthol Natural

Methyl Salicilate

Peppermint oil

Menthol Crystal

Inactive Ingredients:

Aloe extract, Vitamin E Oil ,Lavender Flos,Angelicae Sinesis Rx, Cauda,Salviae,Miltiorrhiza, Chuanxiong, Paeoniae Rubra, Frakinsense, Mrryha, Carthami Flos, Persicae Sm, Cordalis Rz, Nototerygium, Incisum, and Angelica Pubescentis Rx.

PURPOSE

For the relief of minor aches and pains, related to strains and sprains and minor injury.